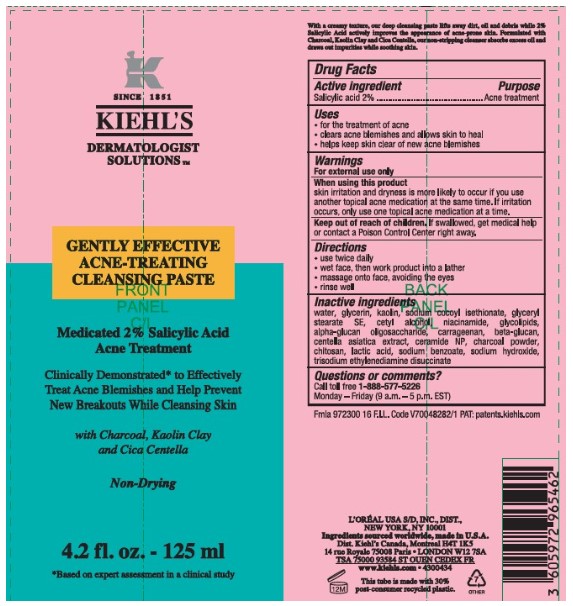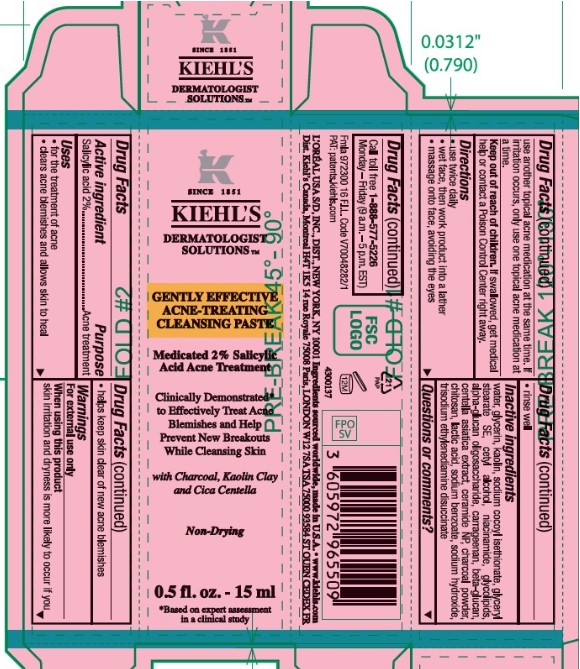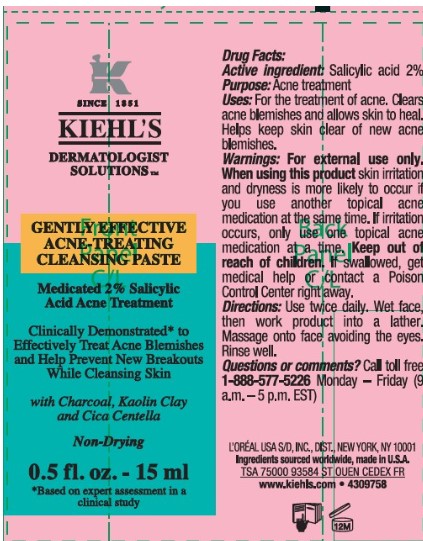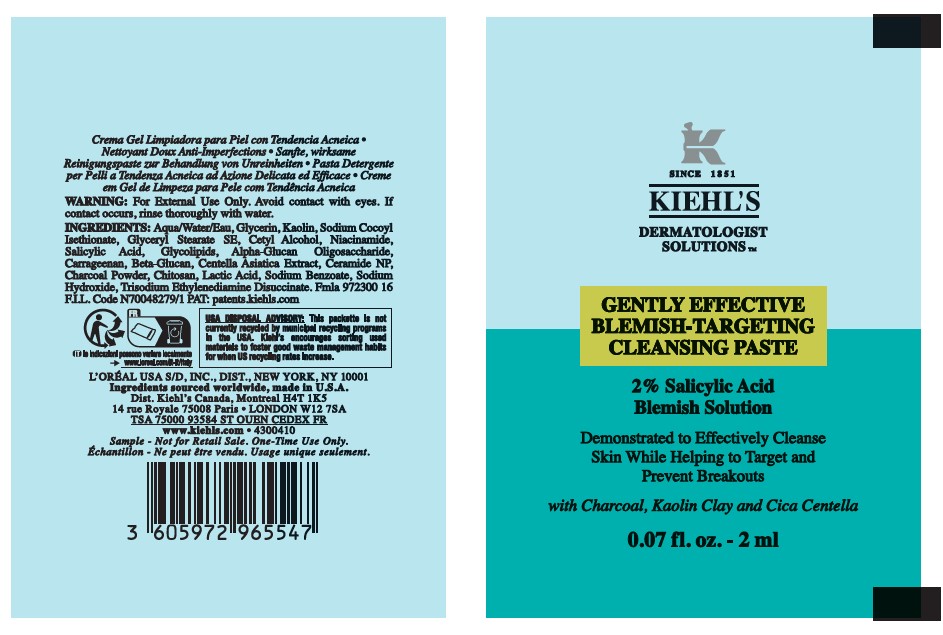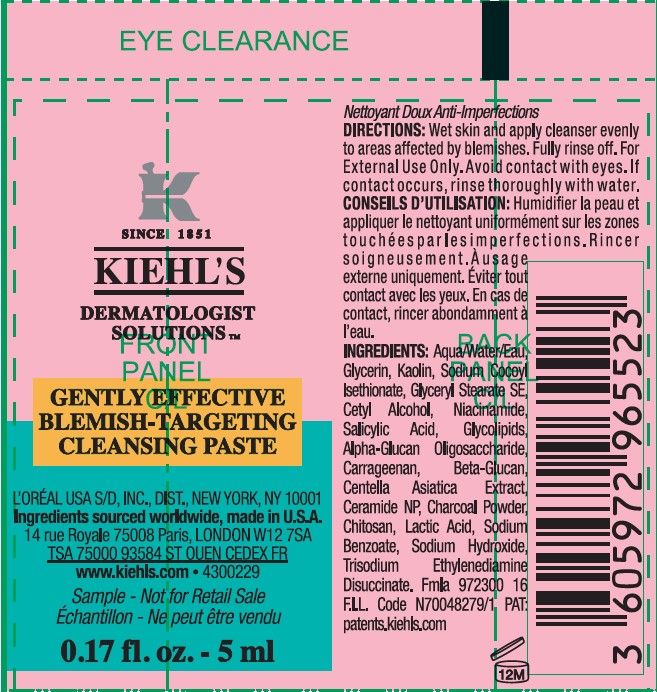 DRUG LABEL: Kiehls Gently Effective Acne Treating Cleansing
NDC: 49967-464 | Form: PASTE
Manufacturer: L'Oreal USA Products Inc
Category: otc | Type: HUMAN OTC DRUG LABEL
Date: 20250328

ACTIVE INGREDIENTS: SALICYLIC ACID 20 mg/1 mL
INACTIVE INGREDIENTS: water; glycerin; kaolin; sodium cocoyl isethionate; glyceryl stearate SE; cetyl alcohol; niacinamide; alpha-glucan oligosaccharide; carrageenan; CENTELLA ASIATICA TRITERPENOIDS; ceramide NP; charcoal powder; POLIGLUSAM; lactic acid; sodium benzoate; sodium hydroxide; trisodium ethylenediamine disuccinate

Drug Facts

Active ingredient

Salicylic acid 2%

Purpose

Acne treatment

Uses

- for the treatment of acne
- clears acne blemishes and allows skin to heal
- helps keep skin clear of new acne blemishes

Warnings

For external use only

When using this product

skin irritation and dryness is more likely to occur if you use another topical acne medication at the same time. If irritation occurs, only use one topical acne medication at a time.

Keep out of reach of children.

If swallowed, get medical help or contact a Poison Control Center right away.

Directions

- use twice daily
- wet face, then work product into a lather
- massage onto face, avoiding the eyes
- rinse well

Inactive ingredients

water, glycerin, kaolin, sodium cocoyl isethionate, glyceryl stearate SE, cetyl alcohol, niacinamide, glycolipids, alpha-glucan oligosaccharide, carrageenan, beta-glucan, centella asiatica extract, ceramide NP, charcoal powder, chitosan, lactic acid, sodium benzoate, sodium hydroxide, trisodium ethylenediamine disuccinate

Questions or comments?

Call toll free 1-888-577-5226

Monday - Friday (9 a.m. - 5 p.m. EST)